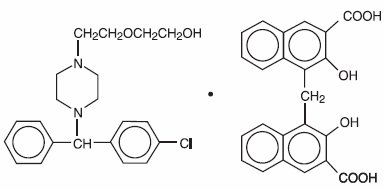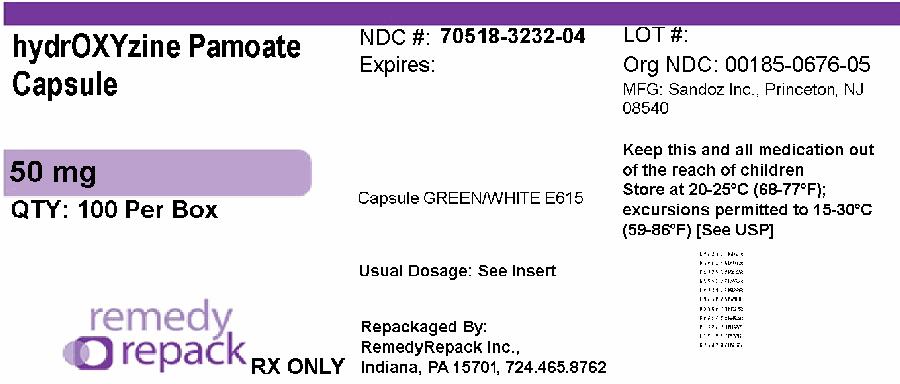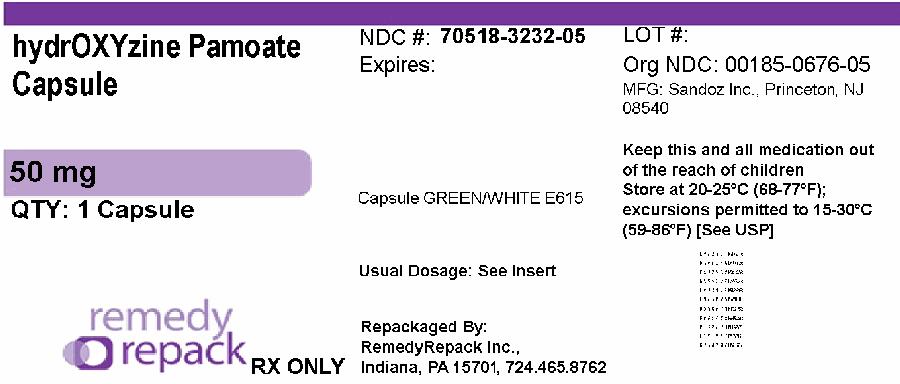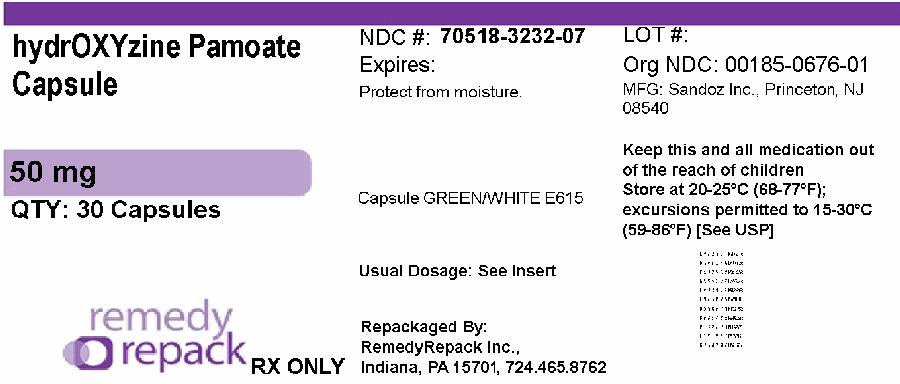 DRUG LABEL: Hydroxyzine pamoate
NDC: 70518-3232 | Form: CAPSULE
Manufacturer: REMEDYREPACK INC.
Category: prescription | Type: HUMAN PRESCRIPTION DRUG LABEL
Date: 20260227

ACTIVE INGREDIENTS: HYDROXYZINE PAMOATE 50 mg/1 1
INACTIVE INGREDIENTS: FD&C BLUE NO. 1; FD&C BLUE NO. 2; FD&C GREEN NO. 3; FD&C YELLOW NO. 6; D&C YELLOW NO. 10; FD&C RED NO. 40; FERROSOFERRIC OXIDE; GELATIN, UNSPECIFIED; LACTOSE MONOHYDRATE; HYDROXYPROPYL CELLULOSE (1600000 WAMW); MAGNESIUM STEARATE; PROPYLENE GLYCOL; SHELLAC; SILICON DIOXIDE; SODIUM LAURYL SULFATE; SODIUM STARCH GLYCOLATE TYPE A POTATO; TITANIUM DIOXIDE

Hydroxyzine Pamoate Capsules, USP

DESCRIPTION

Hydroxyzine pamoate is a light yellow, practically odorless powder practically insoluble in water and methanol and freely soluble in dimethylformamide. It is chemically designated as (±)-2-[2-[4-(p-Chloro-α-phenylbenzyl)-1-piperazinyl]ethoxy]ethanol 4,4’-methylenebis[3-hydroxy-2-naphthoate] (1:1) [10246-75-0] and can be structurally represented as follows:

C21H27CIN2O2•C23H16O6

M.W. 763.27

Each capsule, for oral administration, contains hydroxyzine pamoate equivalent to hydroxyzine hydrochloride 25 mg or 50 mg.

In addition, each capsule contains the following inactive ingredients: colloidal silicon dioxide, hydroxypropyl cellulose, lactose monohydrate, magnesium stearate, sodium starch glycolate (potato), and sodium lauryl sulfate.

The capsule shell contains the following ingredients: D&C Yellow #10, FD&C Green #3, FD&C Yellow #6, gelatin, and titanium dioxide.

The edible imprinting ink contains the following ingredients: black iron oxide, D&C Yellow #10, FD&C Blue #1, FD&C Blue #2, FD&C Red #40, propylene glycol, and shellac glaze.

CLINICAL PHARMACOLOGY

Hydroxyzine pamoate is unrelated chemically to the phenothiazines, reserpine, meprobamate, or the benzodiazepines.

Hydroxyzine pamoate is not a cortical depressant, but its action may be due to a suppression of activity in certain key regions of the subcortical area of the central nervous system. Primary skeletal muscle relaxation has been demonstrated experimentally. Bronchodilator activity, and antihistaminic and analgesic effects have been demonstrated experimentally and confirmed clinically.

An antiemetic effect, both by the apomorphine test and the veriloid test, has been demonstrated. Pharmacological and clinical studies indicate that hydroxyzine in therapeutic dosage does not increase gastric secretion or acidity and in most cases has mild antisecretory activity.

Hydroxyzine is rapidly absorbed from the gastrointestinal tract and hydroxyzine pamoate clinical effects are usually noted within 15 to 30 minutes after oral administration.

INDICATIONS

For symptomatic relief of anxiety and tension associated with psychoneurosis and as an adjunct in organic disease states in which anxiety is manifested.

Useful in the management of pruritus due to allergic conditions such as chronic urticaria and atopic and contact dermatoses, and in histamine-mediated pruritus.

As a sedative when used as premedication and following general anesthesia, hydroxyzine may potentiate meperidine (Demerol®) and barbiturates, so their use in pre-anesthetic adjunctive therapy should be modified on an individual basis. Atropine and other belladonna alkaloids are not affected by the drug. Hydroxyzine is not known to interfere with the action of digitalis in any way and it may be used concurrently with this agent.

The effectiveness of hydroxyzine as an antianxiety agent for long-term use, that is, more than 4 months, has not been assessed by systematic clinical studies. The physician should reassess periodically the usefulness of the drug for the individual patient.

CONTRAINDICATIONS

Hydroxyzine, when administered to the pregnant mouse, rat, and rabbit, induced fetal abnormalities in the rat and mouse at doses substantially above the human therapeutic range. Clinical data in human beings are inadequate to establish safety in early pregnancy. Until such data are available, hydroxyzine is contraindicated in early pregnancy.

Hydroxyzine is contraindicated in patients with a prolonged QT interval.

Hydroxyzine pamoate is contraindicated for patients who have shown a previous hypersensitivity to any component of this medication.

Hydroxyzine is contraindicated in patients with known hypersensitivity to hydroxyzine products, and in patients with known hypersensitivity to cetirizine hydrochloride or levocetirizine hydrochloride.

WARNINGS

Nursing Mothers

It is not known whether this drug is excreted in human milk. Since many drugs are so excreted, hydroxyzine should not be given to nursing mothers.

PRECAUTIONS

THE POTENTIATING ACTION OF HYDROXYZINE MUST BE CONSIDERED WHEN THE DRUG IS USED IN CONJUNCTION WITH CENTRAL NERVOUS SYSTEM DEPRESSANTS SUCH AS NARCOTICS, NON-NARCOTIC ANALGESICS AND BARBITURATES. Therefore, when central nervous system depressants are administered concomitantly with hydroxyzine, their dosage should be reduced. Since drowsiness may occur with use of the drug, patients should be warned of this possibility and cautioned against driving a car or operating dangerous machinery while taking hydroxyzine pamoate. Patients should be advised against the simultaneous use of other CNS depressant drugs, and cautioned that the effect of alcohol may be increased.

QT Prolongation/Torsade de Pointes (TdP)

Cases of QT prolongation and Torsade de Pointes have been reported during post-marketing use of hydroxyzine. The majority of reports occurred in patients with other risk factors for QT prolongation/TdP (pre-existing heart disease, electrolyte imbalances or concomitant arrhythmogenic drug use). Therefore, hydroxyzine should be used with caution in patients with risk factors for QT prolongation, congenital long QT syndrome, a family history of long QT syndrome, other conditions that predispose to QT prolongation and ventricular arrhythmia, as well as recent myocardial infarction, uncompensated heart failure, and bradyarrhythmias.

Caution is recommended during the concomitant use of drugs known to prolong the QT interval. These include Class 1A (e.g., quinidine, procainamide) or Class III (e.g., amiodarone, sotalol) antiarrhythmics, certain antipsychotics (e.g., ziprasidone, iloperidone, clozapine, quetiapine, chlorpromazine), certain antidepressants (e.g., citalopram, fluoxetine), certain antibiotics (e.g., azithromycin, erythromycin, clarithromycin, gatifloxacin, moxifloxacin); and others (e.g., pentamidine, methadone, ondansetron, droperidol).

Acute Generalized Exanthematous Pustulosis (AGEP)

Hydroxyzine may rarely cause acute generalized exanthematous pustulosis (AGEP), a serious skin reaction characterized by fever and numerous small, superficial, non-follicular, sterile pustules, arising within large areas of edematous erythema. Inform patients about the signs of AGEP, and discontinue hydroxyzine at the first appearance of a skin rash, worsening of pre-existing skin reactions which hydroxyzine may be used to treat, or any other sign of hypersensitivity. If signs or symptoms suggest AGEP, use of hydroxyzine should not be resumed and alternative therapy should be considered. Avoid cetirizine or levocetirizine in patients who have experienced AGEP or other hypersensitivity reactions with hydroxyzine, due to the risk of cross-sensitivity.

Geriatric Use

A determination has not been made whether controlled clinical studies of hydroxyzine pamoate included sufficient numbers of subjects aged 65 and over to define a difference in response from younger subjects. Other reported clinical experience has not identified differences in responses between the elderly and younger patients. In general, dose selection for an elderly patient should be cautious, usually starting at the low end of the dosing range, reflecting the greater frequency of decreased hepatic, renal or cardiac function and of concomitant disease or other drug therapy.

The extent of renal excretion of hydroxyzine pamoate has not been determined. Because elderly patients are more likely to have decreased renal function, care should be taken in dose selections.

Sedating drugs may cause confusion and over sedation in the elderly; elderly patients generally should be started on low doses of hydroxyzine pamoate and observed closely.

ADVERSE REACTIONS

Side effects reported with the administration of hydroxyzine pamoate are usually mild and transitory in nature.

Skin and Appendages

Oral hydroxyzine hydrochloride is associated with Acute Generalized Exanthematous Pustulosis (AGEP) and fixed drug eruptions in post-marketing reports.

Anticholinergic

Dry mouth.

Central Nervous System

Drowsiness is usually transitory and may disappear in a few days of continued therapy or upon reduction of the dose. Involuntary motor activity, including rare instances of tremor and convulsions, has been reported, usually with doses considerably higher than those recommended. Clinically significant respiratory depression has not been reported at recommended doses.

Cardiac System

QT prolongation, Torsade de Pointes.

In post-marketing experience, the following additional undesirable effects have been reported:

Body as a Whole

Allergic reaction

Nervous System

Headache

Psychiatric

Hallucination

Skin and Appendages

Pruritus, rash, urticaria

To report SUSPECTED ADVERSE REACTIONS, contact Sandoz Inc. at 1-800-525-8747 or FDA at 1-800-FDA-1088 or www.fda.gov/medwatch.

OVERDOSAGE

The most common manifestation of overdosage of hydroxyzine pamoate is hypersedation. Other reported signs and symptoms were convulsions, stupor, nausea and vomiting. As in the management of overdosage with any drug, it should be borne in mind that multiple agents may have been taken.

If vomiting has not occurred spontaneously, it should be induced. Immediate gastric lavage is also recommended. General supportive care, including frequent monitoring of the vital signs and close observation of the patient, is indicated. Hypotension, though unlikely, may be controlled with intravenous fluids and vasopressors (do not use epinephrine as hydroxyzine counteracts its pressor action). Caffeine and Sodium Benzoate Injection, USP, may be used to counteract central nervous system depressant effects.

Hydroxyzine overdose may cause QT prolongation and Torsade de Pointes. ECG monitoring is recommended in cases of hydroxyzine overdose.

There is no specific antidote. It is doubtful that hemodialysis would be of any value in the treatment of overdosage with hydroxyzine. However, if other agents such as barbiturates have been ingested concomitantly, hemodialysis may be indicated. There is no practical method to quantitate hydroxyzine in body fluids or tissue after its ingestion or administration.

DOSAGE

For symptomatic relief of anxiety and tension associated with psychoneurosis and as an adjunct in organic disease states in which anxiety is manifested: in adults, 50 mg to 100 mg q.i.d.; children under 6 years, 50 mg daily in divided doses; and over 6 years, 50 mg to 100 mg daily in divided doses.

For use in the management of pruritus due to allergic conditions such as chronic urticaria and atopic and contact dermatoses, and in histamine-mediated pruritus: in adults, 25 mg t.i.d. or q.i.d.; children under 6 years, 50 mg daily in divided doses; and over 6 years, 50 mg to 100 mg daily in divided doses.

As a sedative when used as a premedication and following general anesthesia: 50 mg to 100 mg in adults, and 0.6 mg/kg in children. When treatment is initiated by the intramuscular route of administration, subsequent doses may be administered orally.

As with all medications, the dosage should be adjusted according to the patient’s response to therapy.

HOW SUPPLIED

Hydroxyzine Pamoate Capsules, USP, for oral administration, are available as

50 mg

(equivalent to 50 mg hydroxyzine hydrochloride) are dark green/white capsules imprinted “E 615” and supplied as:

NDC: 70518-3232-00

NDC: 70518-3232-01

NDC: 70518-3232-02

NDC: 70518-3232-03

NDC: 70518-3232-04

NDC: 70518-3232-05

NDC: 70518-3232-06

NDC: 70518-3232-07

PACKAGING: 60 in 1 BOTTLE PLASTIC

PACKAGING: 100 in 1 BOX

PACKAGING: 1 in 1 POUCH

PACKAGING: 30 in 1 BLISTER PACK

PACKAGING: 100 in 1 BOX

PACKAGING: 1 in 1 POUCH

PACKAGING: 30 in 1 BLISTER PACK

Storage

Store at 20° to 25°C (68° to 77°F) [see USP Controlled Room Temperature].

Protect from moisture.

Dispense contents in a tight, light-resistant container as defined in the USP, with a child-resistant closure, as required.

KEEP TIGHTLY CLOSED.

KEEP OUT OF THE REACH OF CHILDREN.

Repackaged and Distributed By:

Remedy Repack, Inc.

625 Kolter Dr. Suite #4 Indiana, PA 1-724-465-8762

PRINCIPAL DISPLAY PANEL

DRUG: Hydroxyzine pamoate

GENERIC: Hydroxyzine Pamoate

DOSAGE: CAPSULE

ADMINSTRATION: ORAL

NDC: 70518-3232-0

NDC: 70518-3232-1

NDC: 70518-3232-2

NDC: 70518-3232-3

NDC: 70518-3232-4

NDC: 70518-3232-5

NDC: 70518-3232-6

NDC: 70518-3232-7

COLOR: green

SHAPE: CAPSULE

SCORE: No score

SIZE: 16 mm

IMPRINT: E615

PACKAGING: 60 in 1 BOTTLE, PLASTIC

PACKAGING: 100 in 1 BOX

PACKAGING: 1 in 1 POUCH

PACKAGING: 30 in 1 BLISTER PACK

PACKAGING: 100 in 1 BOX

PACKAGING: 1 in 1 POUCH

PACKAGING: 21 in 1 BLISTER PACK

PACKAGING: 30 in 1 BLISTER PACK

ACTIVE INGREDIENT(S):

- HYDROXYZINE PAMOATE 50mg in 1

INACTIVE INGREDIENT(S):

- TITANIUM DIOXIDE
- SODIUM LAURYL SULFATE
- SILICON DIOXIDE
- SHELLAC
- PROPYLENE GLYCOL
- MAGNESIUM STEARATE
- HYDROXYPROPYL CELLULOSE (1600000 WAMW)
- SODIUM STARCH GLYCOLATE TYPE A POTATO
- LACTOSE MONOHYDRATE
- FERROSOFERRIC OXIDE
- FD&C RED NO. 40
- D&C YELLOW NO. 10
- FD&C YELLOW NO. 6
- FD&C GREEN NO. 3
- FD&C BLUE NO. 2
- GELATIN, UNSPECIFIED
- FD&C BLUE NO. 1